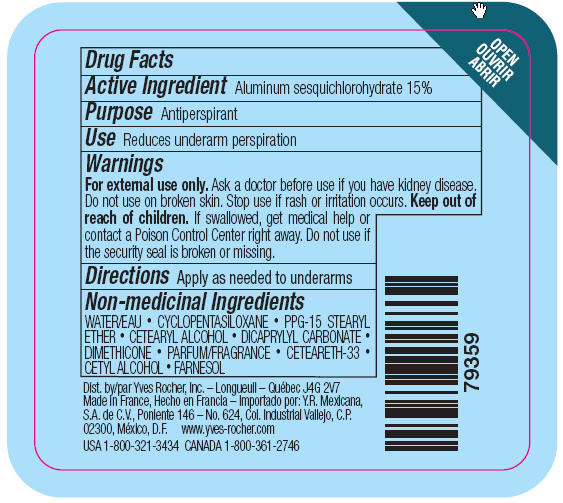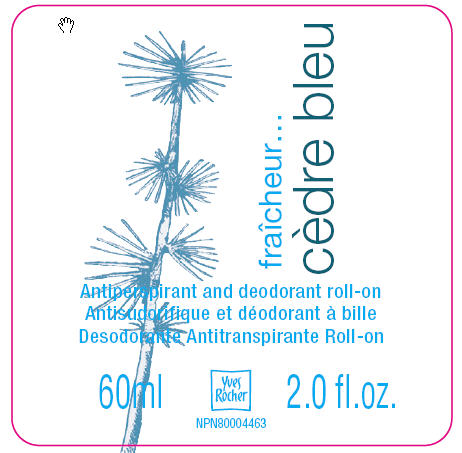 DRUG LABEL: FRAICHEUR CEDRE BLEU ANTIPERSPIRANT AND DEODORANT ROLL-ON
NDC: 54235-206 | Form: LOTION
Manufacturer: Yves Rocher North America Inc. DBA Laboratoire de biologie vegetal Yves Rocher
Category: otc | Type: HUMAN OTC DRUG LABEL
Date: 20110414

ACTIVE INGREDIENTS: ALUMINUM SESQUICHLOROHYDRATE 15 mL/100 mL
INACTIVE INGREDIENTS: WATER 63.5 mL/100 mL; CYCLOMETHICONE 5 8 mL/100 mL; ETHER 4 mL/100 mL; CETOSTEARYL ALCOHOL 3.2 mL/100 mL; DICAPRYLYL CARBONATE 2 mL/100 mL; DIMETHICONE 2 mL/100 mL; CETEARETH-33 0.8 mL/100 mL; CETYL ALCOHOL 0.5 mL/100 mL

Active ingredient
Aluminum sesquichlorohydrate 15%

Purpose
Antiperspirant

Keep out of reach of children. If swallowed, get medical help or contact a Poison Control Center right away.

Use
Reduces underarm perspiration

Warnings:
For external use only. Ask a doctor before use if you have kidney disease. Do not use on broken skin. Stop use if rash or irritation occurs.

Directions:
Apply as needed to underarms

INACTIVE INGREDIENT

Non-medicinal ingredients: WATER • CYCLOPENTASILOXANE • PPG-15 STEARYL ETHER • CETEARYL ALCOHOL • DICAPRYLYL CARBONATE • DIMETHICONE • FRAGRANCE • CETEARETH-33 • CETYL ALCOHOL

PACKAGE LABEL

Fraicheur Cedre bleu
Antiperspirant and deodorant roll-on
60 ml - 2.0 fl. oz.